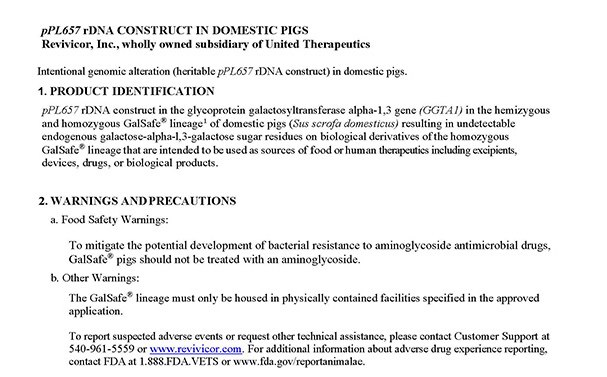 DRUG LABEL: GalSafe
NDC: 86134-001 | Form: NOT APPLICABLE
Manufacturer: Revivicor Inc.
Category: other | Type: INTENTIONAL ANIMAL GENOMIC ALTERATION LABEL
Date: 20241219

ACTIVE INGREDIENTS: pPL657 rDNA construct in the GGTA1 gene in domestic pigs 1 [arb'U]/1 [arb'U]

pPL657 rDNA construct in the GGTA1 gene in domestic pigs

1. PRODUCT IDENTIFICATION

pPL657 rDNA construct in the glycoprotein galactosyltransferase alpha-1,3 gene (GGTA1) in the hemizygous and homozygous GalSafe® [GalSafe® is the registered tradename for Revivicor’s lineage of pigs and is not itself subject to FDA approval. Rather, the regulated article subject to FDA approval is the intentional genomic alteration (pPL657 rDNA construct), which is contained in the GalSafe® lineage of pigs.] lineage of domestic pigs (Sus scrofa domesticus) resulting in undetectable endogenous galactose-alpha-l,3-galactose sugar residues on biological derivatives of the homozygous GalSafe® lineage that are intended to be used as sources of food or human therapeutics including excipients, devices, drugs, or biological products.

2. WARNINGS AND PRECAUTIONS

2. Food Safety Warnings:

a. To mitigate the potential development of bacterial resistance to aminoglycoside antimicrobial drugs, GalSafe® pigs should not be treated with an aminoglycoside.

b. Other Warnings:
The GalSafe® lineage must only be housed in physically contained facilities specified in the approved application.

To report suspected adverse events or request other technical assistance, please contact Customer Support at 540-961-5559 or www.revivicor.com. For additional information about adverse drug experience reporting, contact FDA at 1.888.FDA.VETS or www.fda.gov/reportanimalae.

3. TARGET ANIMAL SAFETY

Data from the GalSafe® lineage demonstrated a lack of adverse effects for the pPL657 rDNA construct in the GalSafe® pigs vs. comparator pigs without an intentional genomic alteration (IGA).

With respect to reproductive outcomes, litter characteristics of GalSafe® pigs were evaluated on a quarterly basis using data collected during 2012-2018. Quarterly means, with standard deviations, and ranges are provided in Table 1 below:

Table 1. Summary statistics for litter characteristics of pigs in the GalSafe® herd based on the summary of quarterly values during 2012-2018 (101 litters and 656 piglets born).
Observation | Mean | Standard Deviation | Minimum | Maximum
Total Piglets Born/Litter (n) | 8.1 | 2.8 | 3.0 | 16.0
Live Piglets at Birth/Litter (n) | 7.4 | 2.9 | 2.0 | 16.0
Mortality at Birth/Litter (n) | 0.8 | 0.7 | 0.0 | 3.0
Pre-Weaning Mortality/Litter (n) | 1.9 | 1.1 | 0.0 | 4.0
Weaned Piglets/Litter (n) | 5.4 | 2.8 | 2.0 | 13.0
Birth Weight/Piglet (lb.) | 2.5 | 0.4 | 1.9 | 3.6
Mortality at Birth (%) | 10.0 | 10.0 | 0.0 | 35.0
Pre-Weaning Mortality (%) | 25.0 | 14.0 | 0.0 | 56.0

Overall morbidity and mortality for post-weaned (growing and breeding populations) GalSafe® pigs were evaluated on a quarterly basis using data collected during 2012-2018. Quarterly means, with standard deviations, and ranges are provided in Table 2 below:

Table 2. Summary statistics for overall morbidity and mortality of post-weaned (growing and breeding populations) GalSafe® pigs based on the summary of quarterly values (2012-2018).
Observation |  | Mean | Standard Deviation | Minimum | Maximum
Mortality | Number of pigs/Quarter (n) | 0.7 | 1.1 | 0.0 | 4.0
Mortality | % | 1.4 | 2.0 | 0.0 | 6.7
Morbiditya | Number of pigs/Quarter (n) | 6.6 | 4.1 | 1.0 | 19.0
Morbiditya | % | 15.3 | 9.8 | 2.6 | 42.9
aoverall morbidity based on recorded therapy (Rx) events for health observations in systems/categories such as the following: reproductive, lameness (hoof, limbs), respiratory, gastrointestinal, skin/integument, or central nervous system

In a study to compare physiological endpoints in GalSafe® pigs vs. comparator pigs (comparators) without an intentional genomic alteration (IGA), blood samples were collected for evaluations. No differences between GalSafe® and comparators were evident based on the following evaluations: serology, CBC (complete blood count) and comprehensive blood chemistry. Values were within expected physiological ranges.

4. EFFECTIVENESS

Multiple generations of the GalSafe® line have demonstrated genetic consistency as established through genetic tests for the presence of the pPL657 rDNA construct, pPL657 rDNA sequence fidelity and pPL657 rDNA construct integration site consistency. For multiple consecutive generations, phenotypic consistency has been established based on the undetectable levels of galactose-alpha-1,3-galactose sugar residues on biological derivatives of homozygous GalSafe® pigs.

Produced by:
Revivicor, Inc., wholly owned subsidiary of
United Therapeutics
1700 Kraft Dr, Suite 2400
Blacksburg, VA 24060 USA

Customer Support: 540-961-5559 www.revivicor.com

Approved by FDA under NADA #141-542